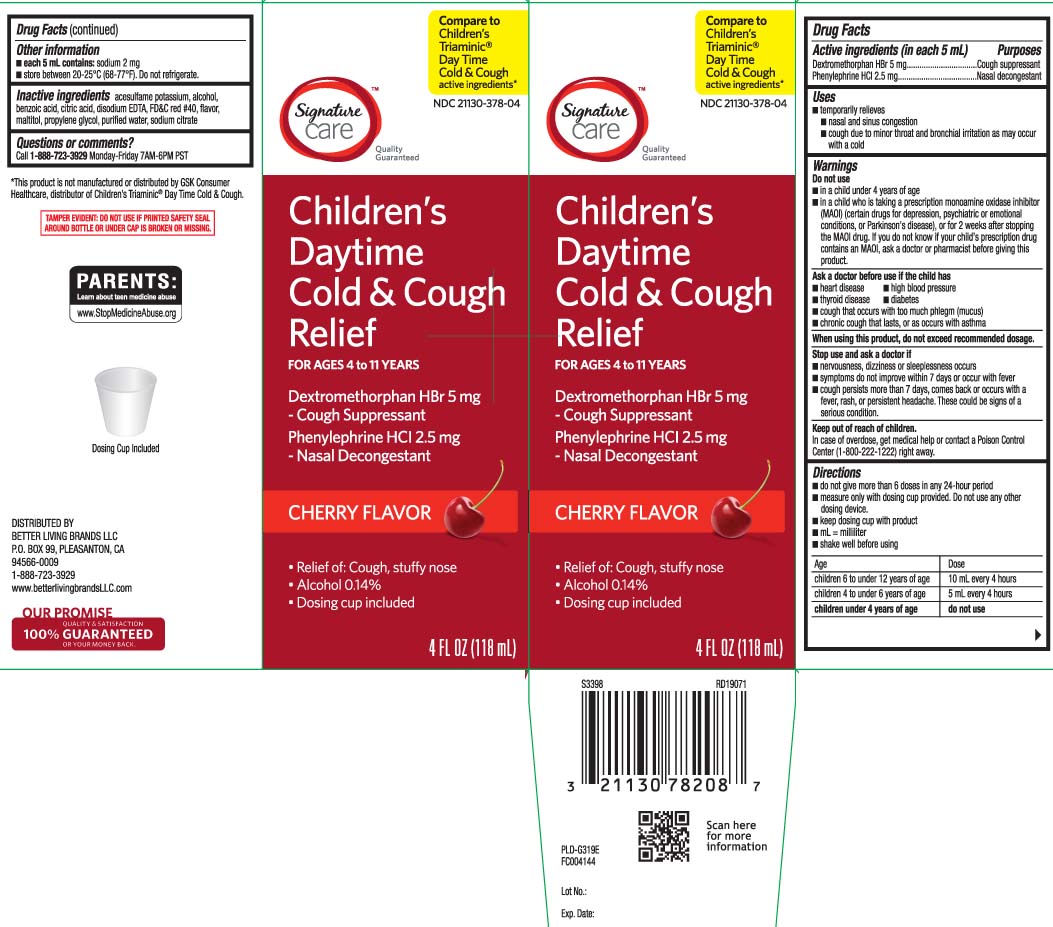 DRUG LABEL: Triacting Daytime Cold Cough
NDC: 21130-378 | Form: SYRUP
Manufacturer: Safeway, Inc.
Category: otc | Type: HUMAN OTC DRUG LABEL
Date: 20240515

ACTIVE INGREDIENTS: DEXTROMETHORPHAN HYDROBROMIDE 5 mg/5 mL; PHENYLEPHRINE HYDROCHLORIDE 2.5 mg/5 mL
INACTIVE INGREDIENTS: ACESULFAME POTASSIUM; ALCOHOL; BENZOIC ACID; ANHYDROUS CITRIC ACID; EDETATE DISODIUM; FD&C RED NO. 40; MALTITOL; PROPYLENE GLYCOL; WATER; SODIUM CITRATE

Drug Facts

Active ingredients (in each 5 mL)

Dextromethorphan HBr 5 mg

Phenylephrine HCl 2.5 mg

Purposes

Cough suppressant

Nasal decongestant

Uses

- temporarily relieves:
  - nasal and sinus congestion
  - cough due to minor throat and bronchial irritation as may occur with a cold

Warnings

Do not use

- in a child under 4 years of age
- in a child who is taking a prescription monoamine oxidase inhibitor (MAOI) (certain drugs for depression, psychiatric or emotional conditions, or Parkinson’s disease), or for 2 weeks after stopping the MAOI drug. If you do not know if the child’s prescription drug contains an MAOI, ask a doctor or pharmacist before giving this product.

Ask a doctor before use if the child has

- heart disease
- high blood pressure
- thyroid disease
- diabetes
- cough that occurs with too much phlegm (mucus)
- chronic cough that lasts, or as occurs with asthma

When using this product,

do not exceed recommended dosage

Stop use and ask a doctor if

- nervousness, dizziness or sleeplessness occurs
- symptoms do not improve within 7 days or occur with a fever
- cough persists for more than 7 days, comes back or occurs with a fever, rash or persistent headache. These could be signs of a serious condition.

Keep out of reach of children.

In case of overdose, get medical help or contact a Poison Control Center (1-800-222-1222) right away.

Directions

- do not take more than 6 doses in any 24-hour period
- measure only with dosing cup provided. Do not use any other dosing device
- keep dosing cup with product
- mL = milliliter
- shake well before using

age | dose
children 6 to under 12 years of age | 10 mL every 4 hours
children 4 to 6 years of age | 5 mL every 4 hours
children under 4 years of age | do not use

Other information

- each 5 mL contains: sodium 2 mg
- store between 20-25°C (68-77°F). Do not refrigerate.

Inactive ingredients

acesulfame potassium, alcohol, benzoic acid, citric acid, disodium EDTA, FD&C red #40, maltitol, flavor, propylene glycol, purified water, sodium citrate

Questions or comments?

Call 1-888-723-3929 Monday-Friday 7AM-6PM PST

Principal Display Panel

Compare to Children's Triaminic® Day Time Cold & Cough active ingredients*

Children's Daytime

Cold & Cough Relief

FOR AGES 4-11 YEARS

Dextromethorphan HBr 5 mg-Cough suppressant

Phenylephrine HCl 2.5 mg-Nasal decongestant

- Relief of: Cough, stuffy nose
- Alcohol 0.14%
- Dosing cup included

CHERRY FLAVOR

FL OZ (mL)

*This product is not manufactured or distributed by GSK Consumer Health, distributors of Children's Triaminic® DayTime Cold & Cough.

TAMPER EVIDENT: DO NOT USE IF PRINTED SAFETY SEAL AROUND BOTTLE OR UNDER CAP IS BROKEN OR MISSING

DISTRIBUTED BY

BETTER LIVING BRANDS LLC

P.O. BOX 99, PLEASANTON, CA

94566-0009

www.betterlivingbrandsLLC.com

Package Label

SIGNATURE CARE Children's Daytime Cold & Cough Relief